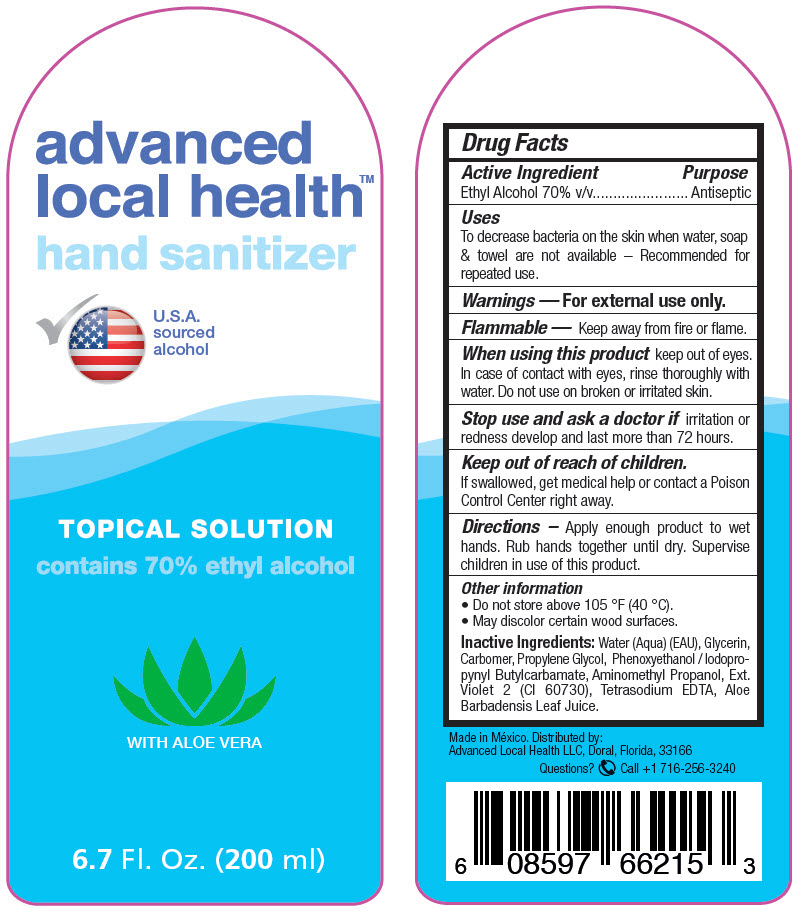 DRUG LABEL: Advanced Local Health Hand Sanitizer
NDC: 74264-002 | Form: GEL
Manufacturer: Advanced Local Health LLC
Category: otc | Type: HUMAN OTC DRUG LABEL
Date: 20200806

ACTIVE INGREDIENTS: Alcohol 70 mL/100 mL
INACTIVE INGREDIENTS: water; CARBOMER HOMOPOLYMER, UNSPECIFIED TYPE; GLYCERIN; PROPYLENE GLYCOL; PHENOXYETHANOL; AMINOMETHYLPROPANOL; EXT. D&C VIOLET NO. 2; EDETATE SODIUM; ALOE VERA LEAF; IODOPROPYNYL BUTYLCARBAMATE

Advanced Local Health™ Hand Sanitizer

Drug Facts

Active Ingredient

Ethyl Alcohol 70% v/v

Purpose

Antiseptic

Uses

To decrease bacteria on the skin when water, soap & towel are not available – Recommended for repeated use.

Warnings

For external use only.

Flammable

Keep away from fire or flame.

When using this product keep out of eyes. In case of contact with eyes, rinse thoroughly with water. Do not use on broken or irritated skin.

Stop use and ask a doctor if irritation or redness develop and last more than 72 hours.

Keep out of reach of children.

If swallowed, get medical help or contact a Poison Control Center right away.

Directions

Apply enough product to wet hands. Rub hands together until dry. Supervise children in use of this product.

Other information

- Do not store above 105 °F (40 °C).
- May discolor certain wood surfaces.

Inactive Ingredients

Water (Aqua) (EAU), Glycerin, Carbomer, Propylene Glycol, Phenoxyethanol / Iodopropynyl Butylcarbamate, Aminomethyl Propanol, Ext. Violet 2 (CI 60730), Tetrasodium EDTA, Aloe Barbadensis Leaf Juice.

Questions?

Call +1 716-256-3240

Distributed by:
Advanced Local Health LLC, Doral, Florida, 33166

PRINCIPAL DISPLAY PANEL - 200 ml Bottle Label

advanced
local health™
hand sanitizer

U.S.A.
sourced
alcohol

TOPICAL SOLUTION
contains 70% ethyl alcohol

WITH ALOE VERA

6.7 Fl. Oz. (200 ml)